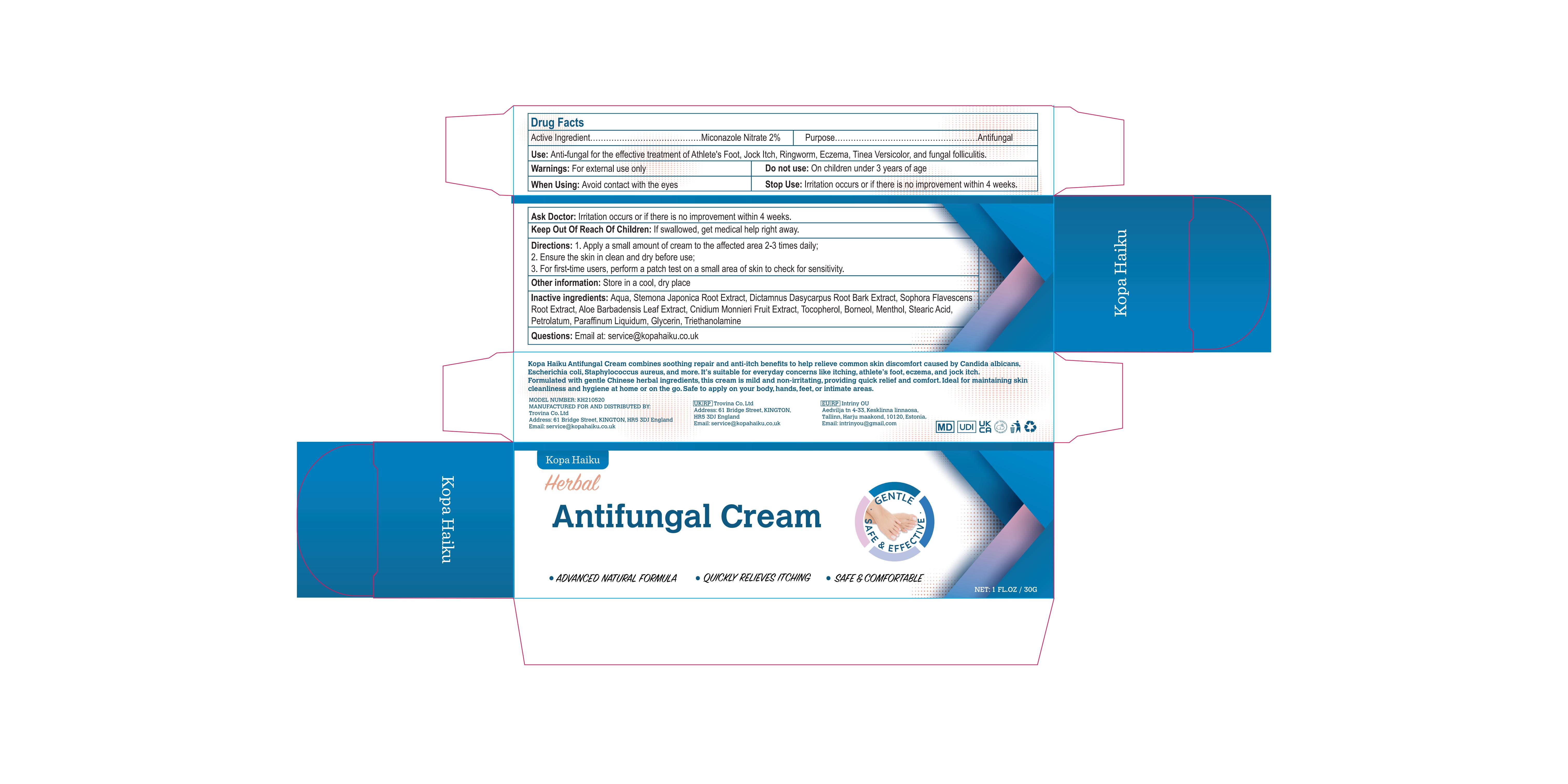 DRUG LABEL: Kopa Haiku Antifungal Cream
NDC: 87041-002 | Form: CREAM
Manufacturer: Trovina Co. Ltd
Category: otc | Type: HUMAN OTC DRUG LABEL
Date: 20260212

ACTIVE INGREDIENTS: MICONAZOLE NITRATE 20 mg/1 g
INACTIVE INGREDIENTS: ALOE BARBADENSIS LEAF; PARAFFINUM LIQUIDUM; DICTAMNUS DASYCARPUS ROOT BARK; TOCOPHEROL; SOPHORA FLAVESCENS ROOT; GLYCERIN; CNIDIUM MONNIERI FRUIT; BORNEOL; PETROLATUM; STEARIC ACID; TRIETHANOLAMINE; STEMONA JAPONICA ROOT; MENTHOL; AQUA

ACTIVE INGREDIENT

Miconazole Nitrate 2%

PURPOSE

Antifungal

INDICATIONS AND USAGE

Anti-fungal for the effective treatment of Athlete's Foot, Jock Itch, Ringworm, Eczema, Tinea Versicolor, and fungal folliculitis.

WARNINGS

For external use only

DO NOT USE

On children under 3 years of age.

OTHER SAFETY INFORMATION

Avoid contact with the eyes.

STOP USE

Irritation occurs or if there is no improvement within 4 weeks.

Keep out of reach of children. In case of ingestion, seek medical help or contact a Poison Control Center immediately.

DOSAGE AND ADMINISTRATION

1 Apply a small amount of cream to the affected area 2-3 times daily; 2 Ensure the skin in clean and dry before use; 3 For first-time users, perform a patch test on a small area of skin to check for sensitivity.

INACTIVE INGREDIENT

Aqua, Stemona Japonica Root Extract, Dictamnus Dasycarpus Root Bark Extract, Sophora Flavescens Root Extract, Aloe Barbadensis Leaf Extract, Cnidium Monnieri Fruit Extract, Tocopherol, Borneol, Menthol, Stearic Acid, Petrolatum, Paraffinum Liquidum, Glycerin, Triethanolamine

STORAGE AND HANDLING

Store in a cool, dry place.

QUESTIONS

Email at: service@kopahaiku.co.uk